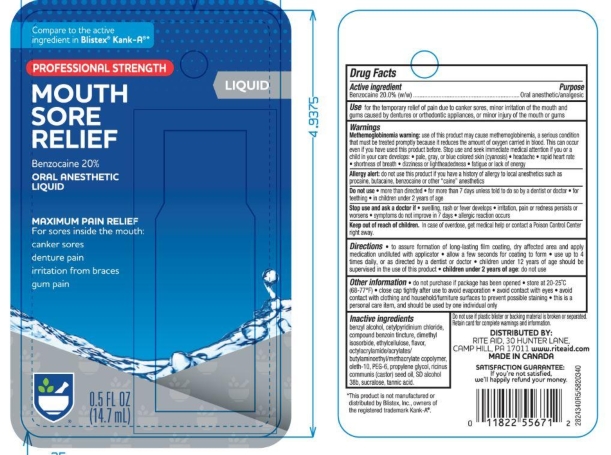 DRUG LABEL: Rite Aid
NDC: 11822-5340 | Form: LIQUID
Manufacturer: Rite Aid
Category: otc | Type: HUMAN OTC DRUG LABEL
Date: 20251121

ACTIVE INGREDIENTS: BENZOCAINE 20 g/100 g
INACTIVE INGREDIENTS: ALCOHOL; ETHYLCELLULOSES; TANNIC ACID; CETYLPYRIDINIUM CHLORIDE; SUCRALOSE; BENZYL ALCOHOL; PROPYLENE GLYCOL; OLETH-10; DIMETHYL ISOSORBIDE; RICINUS COMMUNIS SEED; WATER; POLYETHYLENE GLYCOL 300; BENZOIN RESIN; MENTHOL

5820340 Rite Aid Prof Str Mouth Pain Liq

Active ingredient

Benzocaine 20.0% ...................................................................... Oral anesthetic / analgesic

Use

for the temporary relief of pain due to canker sores, minor irritation of the mouth and gums caused by dentures or orthodontic appliances, or minor injury of the mouth or gums

WARNINGS

For oral use only
Allergy alert: do not use this product if you have a history of allergy to local anesthetics such as procaine, butacaine, benzocaine or other “caine” anesthetics
When using this product Do not use for more than 7 days unless told to do so by a dentist or doctor If sore mouth symptoms do not improve in 7 days; if irritation, pain or redness persists or worsens; or, if swelling, rash or fever develops, see your doctor or dentist promptly. Do not exceed recommended dosage.

Keep out of reach of children. In case of overdose, get medical help or contact a Poison Control
Center right away.

Directions

to assure formation of long lasting film coating, dry affected area and apply
medication undiluted with applicator. allow a few seconds for coating to form. use up to 4 times
daily, or as directed by a dentist or doctor. children 12 years of age should be supervised in
the use of this product. children under 2 years of age:ask a dentist or doctor

DOSAGE AND ADMINISTRATION

• use up to 4 times daily, or as directed by a dentist or doctor • children under 12 years of age should be supervised in the use of this product • children under 2 years of age: consult a dentist or doctor

Other Information

do not purchase if package has been opened
store at 20 - 25 C (68-77F)
close cap tightly after use to avoid evaporation
avoid contact with eyes
avoid contact with clothing and household furniture surfaces to avoid possible staining
this is a personal care item, and should be used by one individual only

Inactive ingredients

Benzyl Alcohol, Cetylpyridinium
Chloride, Compound Benzoin Tincture,
Dimethyl Isosorbide, Ethylcellulose,
Flavor, Octylacrylamideacrylates/
butylaminoethyl/methacrylate
Copolymer, Oleth-10, PEG-6, Propylene
Glycol, Ricinus Communis (Castor)
Seed Oil, SD Alcohol 38B, Sucralose,
Tannic Acid.